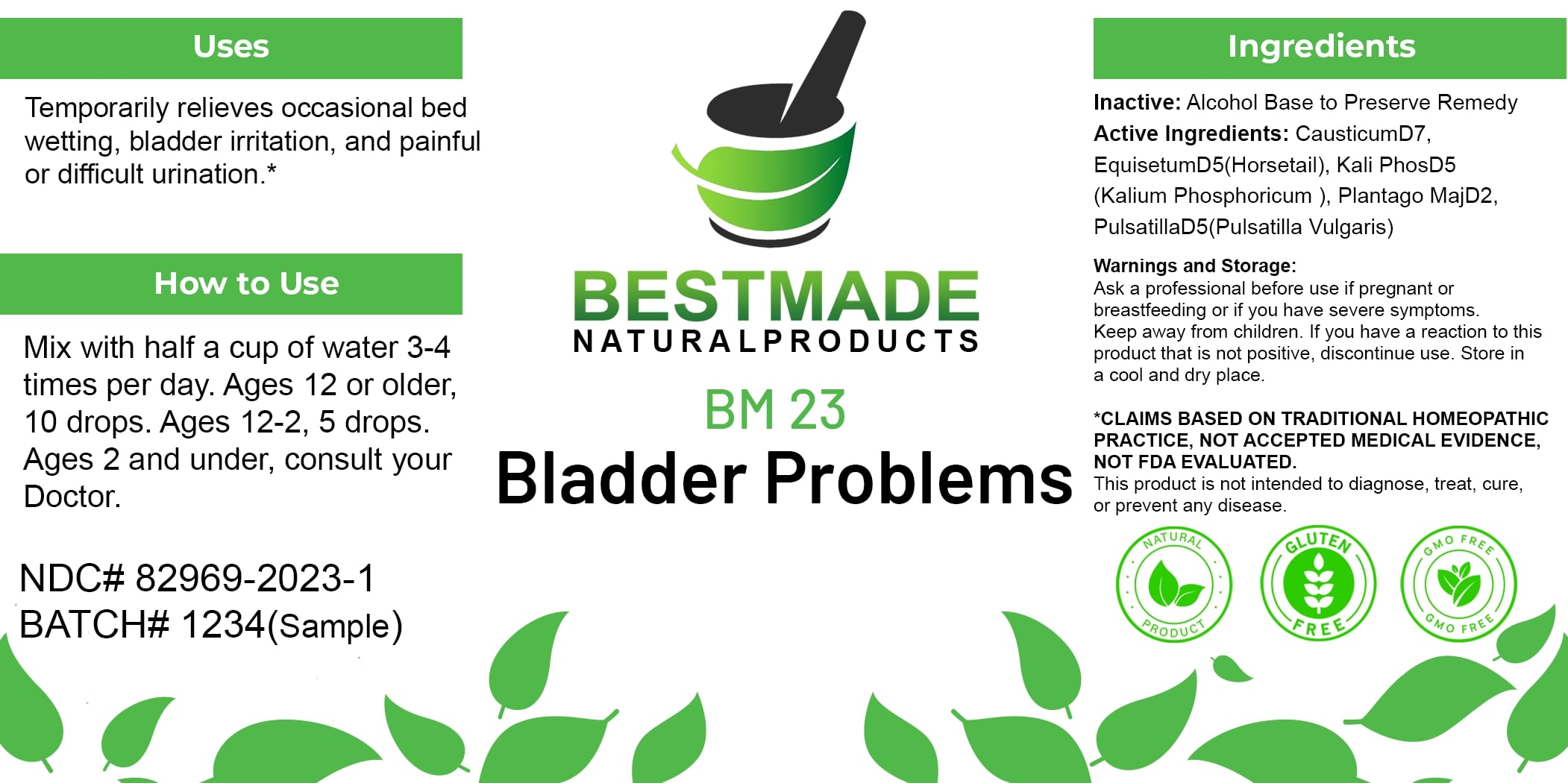 DRUG LABEL: Bestmade Natural Products BM23
NDC: 82969-2023 | Form: LIQUID
Manufacturer: Bestmade Natural Products
Category: homeopathic | Type: HUMAN OTC DRUG LABEL
Date: 20250123

ACTIVE INGREDIENTS: POTASSIUM PHOSPHATE, UNSPECIFIED FORM 30 [hp_C]/30 [hp_C]; CAUSTICUM 30 [hp_C]/30 [hp_C]; ATROPA BELLADONNA 30 [hp_C]/30 [hp_C]; PLANTAGO MAJOR 30 [hp_C]/30 [hp_C]; PULSATILLA PRATENSIS WHOLE 30 [hp_C]/30 [hp_C]; EQUISETUM HYEMALE 30 [hp_C]/30 [hp_C]
INACTIVE INGREDIENTS: ALCOHOL 30 [hp_C]/30 [hp_C]

BM23

DOSAGE AND ADMINISTRATION

How to Use

Mix with half a cup of water 3-4 times per day. Ages 12 or older, 10 drops. Ages 12-2, 5 drops. Ages 2 and under, consult your Doctor.

INACTIVE INGREDIENT

Ingredients

Inactive: Alcohol Base to Preserve Remedy

Uses

Temporarily relieves occasional bed wetting, bladder irritation, and painful or difficult urination.*

*CLAIMS BASED ON TRADITIONAL HOMEOPATHIC PRACTICE, NOT ACCEPTED MEDICAL EVIDENCE. NOT FDA EVALUATED.

This product is not intended to diagnose, treat, cure, or prevent any disease.

Uses

Temporarily relieves occasional bed wetting, bladder irritation, and painful or difficult urination.*

*CLAIMS BASED ON TRADITIONAL HOMEOPATHIC PRACTICE, NOT ACCEPTED MEDICAL EVIDENCE. NOT FDA EVALUATED.

This product is not intended to diagnose, treat, cure, or prevent any disease.

ACTIVE INGREDIENT

Active Ingredients: Causticum D7, Equisetum D5 (Horsetail), Kali Phos D5 (Kalium Phosphoricum), Plantago Maj D2, Pulsatilla D5 (Pulsatilla Vulgaris)

KEEP OUT OF REACH OF CHILDREN

Warnings and Storage:

Ask a professional before use if pregnant or breastfeeding or if you have severe symptoms. Keep away from children. If you have a reaction to this product that is not positive, discontinue use. Store in a cool and dry place.

Warnings and Storage:

Ask a professional before use if pregnant or breastfeeding or if you have severe symptoms. Keep away from children. If you have a reaction to this product that is not positive, discontinue use. Store in a cool and dry place.

*CLAIMS BASED ON TRADITIONAL HOMEOPATHIC PRACTICE, NOT ACCEPTED MEDICAL EVIDENCE. NOT FDA EVALUATED.

This product is not intended to diagnose, treat, cure, or prevent any disease.

Entire package label